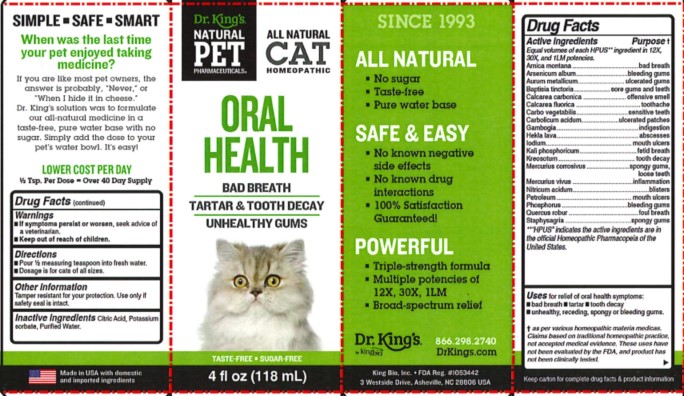 DRUG LABEL: Oral Health
NDC: 57955-4710 | Form: LIQUID
Manufacturer: King Bio Inc.
Category: homeopathic | Type: OTC ANIMAL DRUG LABEL
Date: 20240716

ACTIVE INGREDIENTS: ARNICA MONTANA WHOLE 12 [hp_X]/118 mL; ARSENIC TRIOXIDE 12 [hp_X]/118 mL; GOLD 12 [hp_X]/118 mL; BAPTISIA TINCTORIA ROOT 12 [hp_X]/118 mL; OYSTER SHELL CALCIUM CARBONATE, CRUDE 12 [hp_X]/118 mL; CALCIUM FLUORIDE 12 [hp_X]/118 mL; ACTIVATED CHARCOAL 12 [hp_X]/118 mL; PHENOL 12 [hp_X]/118 mL; GAMBOGE 12 [hp_X]/118 mL; HEKLA LAVA 12 [hp_X]/118 mL; IODINE 12 [hp_X]/118 mL; DIBASIC POTASSIUM PHOSPHATE 12 [hp_X]/118 mL; WOOD CREOSOTE 12 [hp_X]/118 mL; MERCURIC CHLORIDE 12 [hp_X]/118 mL; MERCURY 12 [hp_X]/118 mL; NITRIC ACID 12 [hp_X]/118 mL; KEROSENE 12 [hp_X]/118 mL; PHOSPHORUS 12 [hp_X]/118 mL; QUERCUS ROBUR TWIG BARK 12 [hp_X]/118 mL; DELPHINIUM STAPHISAGRIA SEED 12 [hp_X]/118 mL
INACTIVE INGREDIENTS: CITRIC ACID MONOHYDRATE; POTASSIUM SORBATE; WATER

Oral Health

Warnings

- If symptoms persist or worsen, seek advice of a veterinarian.
- Keep out of reach of children.

Directions

- Pour 1/2 measuring teaspoon into fresh water.
- Dosage is for cats of all sizes.

Other Information

Tamper resistant for your protection.

Use only if safety seal is intact.

Keep carton for complete drug facts and product information.

This product has not been clinically tested.

Questions? Call 866.298.2740

King Bio, Inc. 3 Westside Drive

Asheville, NC, 28806 USA

FDA Reg. #1053442

For latest product information and instructions: www.DrKings.com

Keep out of reach of children.

Active Ingredients

Arnica montana, Arsenicum album, Aurum metallicum, Baptisia tinctoria, Calcarea carbonica, Calcarea fluorica, Carbo vegetabilis, Carbolicum acidum, Gambogia, Hekla lava, Iodium, Kali phosphoricum, Kreosotum, Mercurius corrosivus, Mercurius vivus, Nitricum acidum, Petroleum, Phosphorus, Quercus robur, Staphysagria.

HPUS Indicates the active ingredients are in the official Homeopathic Pharmacopeia of the United States.

Uses

Uses for the relief of oral health symptoms:

- bad breath
- tartar
- tooth decay
- unhealthy, receding, spongy or bleeding gums

As per various homeopathic materia medicas. Claims based on traditional homeopathic pracice, not accepted medical evidence. These uses have not been evaluated by the FDA, and Product has not been clinically tested.

Inactive Ingredient

Citric acid, Potassium sorbate, and Purified water.

PURPOSE

Equal volumes of each HPUS ingredient in 12X, 30X, and 1LM potencies.

Arnica montana................................................bad breath

Arsenicum album.........................................bleeding gums

Aurum metallicum......................................ulcerated gums

Baptisia tinctoria.................................sore gums and teeth

Calcarea carbonica......................................offensive smell

Calcarea fluorica................................................toothache

Carbo vegetabilis.........................................sensitive teeth

Carbolicum acidum..................................ulcerated patches

Gambogia.......................................................indigestion

Hekla lava........................................................abscesses

Iodium........................................................mouth ulcers

Kali phosphoricum..........................................fetid breath

Kreosotum.....................................................tooth decay

Mercurius corrosivus......................................................

................................................spongy gums, loose teeth

Mercurius vivus............................................inflammation

Nitricum acidum....................................................blisters

Petroleum....................................................mouth ulcers

Phosphorus................................................bleeding gums

Quercus robur.................................................foul breath

Staphysagria...............................................spongy gums